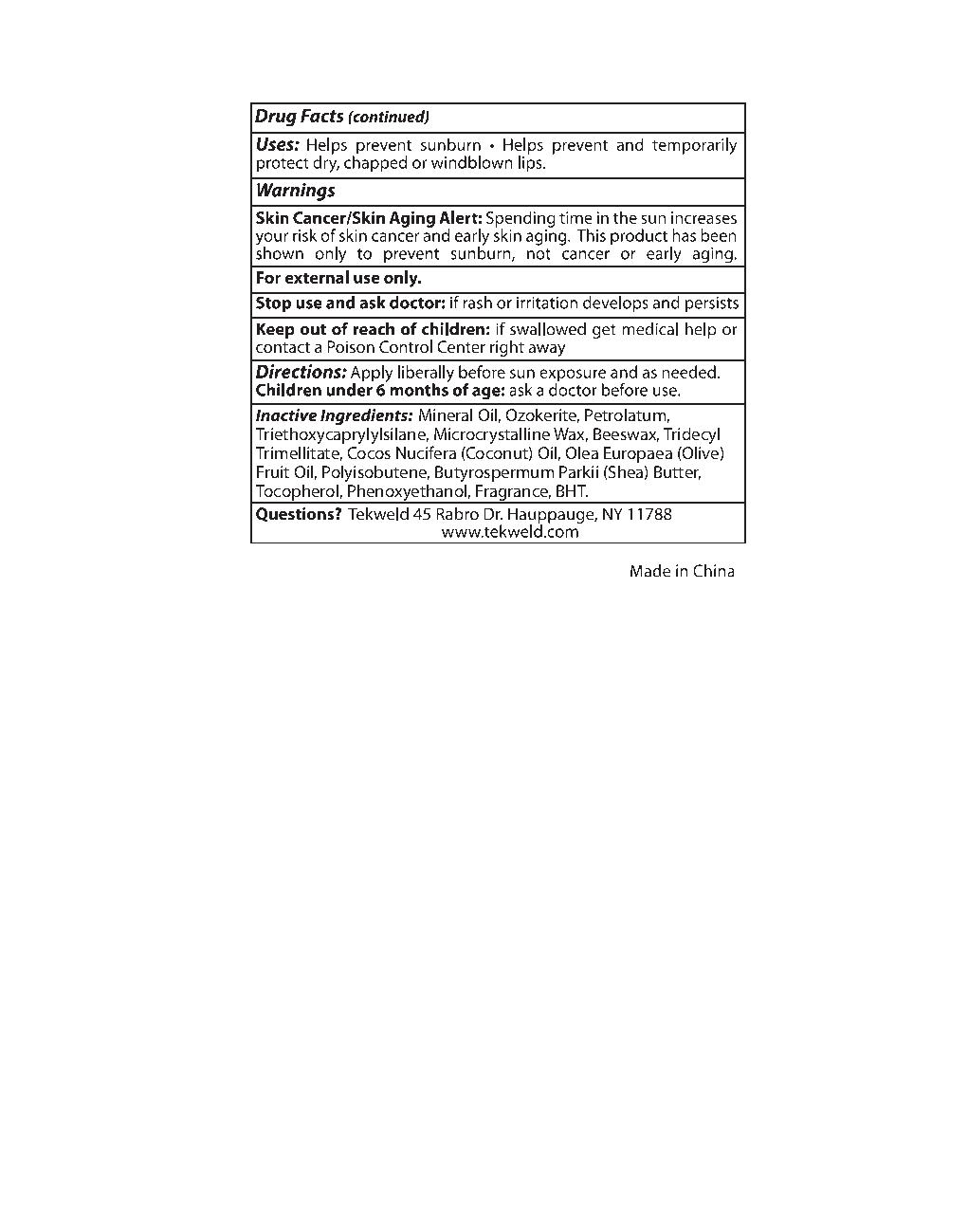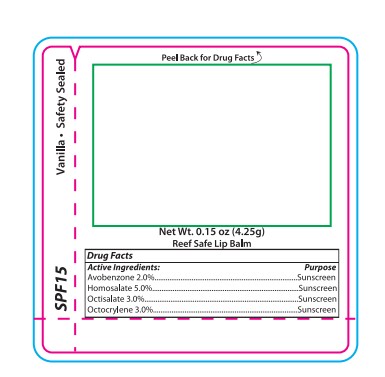 DRUG LABEL: Reef safe lip balm
NDC: 82953-049 | Form: LIPSTICK
Manufacturer: Cosmuses Cosmetics (Ningbo) Co., Ltd.
Category: otc | Type: HUMAN OTC DRUG LABEL
Date: 20260115

ACTIVE INGREDIENTS: OCTOCRYLENE 3 g/100 g; HOMOSALATE 5 g/100 g; AVOBENZONE 2 g/100 g; OCTISALATE 3 g/100 g
INACTIVE INGREDIENTS: PETROLATUM; TRIETHOXYCAPRYLYLSILANE; BHT; MINERAL OIL; BEESWAX; TOCOPHEROL; CERESIN; PHENOXYETHANOL; FRAGRANCE 13576; POLYISOBUTYLENE (1000 MW); COCOS NUCIFERA (COCONUT) OIL; OLEA EUROPAEA (OLIVE) FRUIT OIL; BUTYROSPERMUM PARKII (SHEA) BUTTER; TRIDECYL TRIMELLITATE; MICROCRYSTALLINE WAX

Reef safe lip balm

Drug Facts

Active ingredients

Avobenzone 2%

Homosalate 5%

Octisalate 3%

Octocrylene 3%

Purpose

Sunscreen

Uses

- Helps prevent sunburn
- Helps prevent and temporarily protect dry, chapped or windblown lips.

WARNINGS

For external use only

Skin cancer/ skin aging alert

Spending time in the sun increases your risk of skin cancer and early skin aging. This product has been shown only to prevent sunburn, not cancer or early aging.

WARNINGS

For external use only

Stop use and ask a doctor: if rash or irritation develops and persists.

Keep out of reach of children. If swallowed, get medical help or contact a Poison Control Center right away.

Directions

Apply librerally before sun exposure and as needed.

Children under 6 months or age: ask a doctor before use.

Inactive ingredients

Mineral Oil,Ozokerite, Petrolatum, Triethoxycaprylylsilane, Microcrystalline Wax, Beeswax, Tridecyl Trimellitate, Cocos Nucifera (Coconut) Oil,Olea Europaea (Olive) Fruit Oil,Polyisobutene, Butyrospermum Parkii (Shea) Butter, Tocopherol, Phenoxyethanol,Fragrance, BHT

Questions?

Tekweld 45 Rabro Dr.Hauppauge, NY 11788

www.tekweld.com